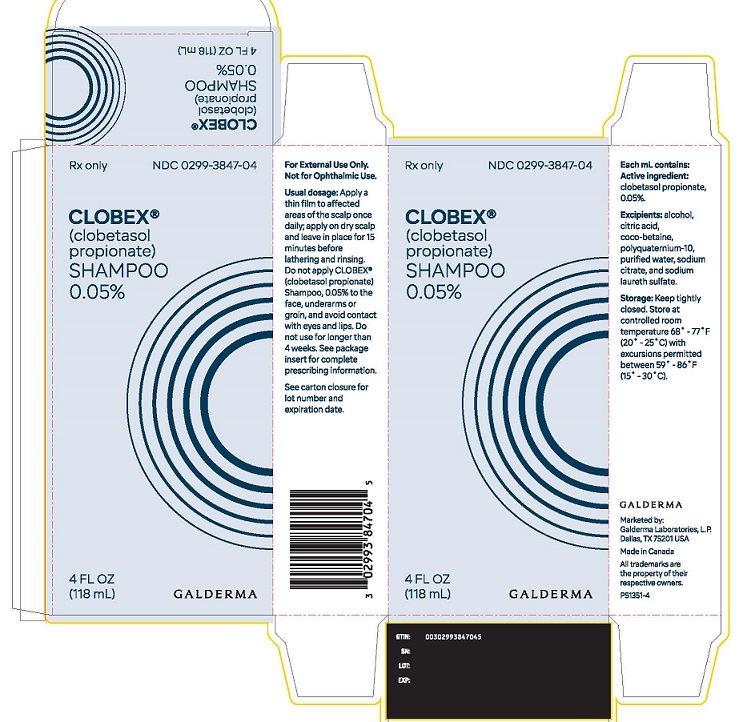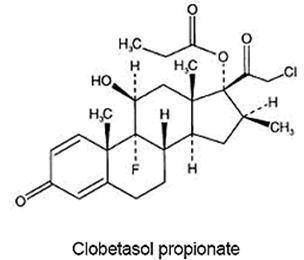 DRUG LABEL: Clobex
NDC: 0299-3847 | Form: SHAMPOO
Manufacturer: Galderma Laboratories, L.P.
Category: prescription | Type: HUMAN PRESCRIPTION DRUG LABEL
Date: 20250821

ACTIVE INGREDIENTS: CLOBETASOL PROPIONATE 0.05 g/100 mL
INACTIVE INGREDIENTS: ALCOHOL; CITRIC ACID MONOHYDRATE; COCO-BETAINE; POLYQUATERNIUM-10 (400 CPS AT 2%); WATER; SODIUM CITRATE; SODIUM LAURETH SULFATE

HIGHLIGHTS OF PRESCRIBING INFORMATION

These highlights do not include all the information needed to use CLOBEX ®Shampoo safely and effectively. See full prescribing information for CLOBEX ®Shampoo.
CLOBEX ®(clobetasol propionate) Shampoo, 0.05% for topical use
Initial U.S. Approval: 1985

1 INDICATIONS AND USAGE

CLOBEX (clobetasol propionate) Shampoo, 0.05% is a corticosteroid indicated for the treatment of moderate to severe scalp psoriasis in subjects 18 years of age and older. (1)
Limitations of Use:

- Do not use on the face, axillae or groin. (1.2)
- Avoid any contact with the eyes and lips. (1.2)

2 DOSAGE AND ADMINISTRATION

- Not for oral, ophthalmic, or intravaginal use. (2)
- CLOBEX Shampoo, 0.05% should be applied onto dry (not wet) scalp once a day in a thin film to the affected areas only, and left in place for 15 minutes before lathering and rinsing. CLOBEX Shampoo, 0.05% contains a super-high potent topical corticosteroid; therefore treatment should be limited to 4 weeks. (2)
- As with other corticosteroids, therapy should be discontinued when control is achieved. (2)
- Total dosage should not exceed 50 g (50mL or 1.75 fl. oz.) per week. (2)
- CLOBEX Shampoo should not be used with a shower cap or bathing cap. (2)

3 DOSAGE FORMS AND STRENGTHS

Shampoo, 0.05% (3)

4 CONTRAINDICATIONS

None (4)

5 WARNINGS AND PRECAUTIONS

Clobetasol propionate is a highly potent topical corticosteroid that has been shown to suppress the hypothalamic-pituitary-adrenal (HPA) axis at the lowest doses tested. (5.1)
Cushing’s syndrome, hyperglycemia and unmasking of latent diabetes mellitus can also result from systemic absorption of topical corticosteroids. (5.1)
Systemic absorption may require periodic evaluation for HPA axis suppression. Modify use if HPA axis suppression develops. (5.1)
Children may be more susceptible to systemic toxicity from use of topical corticosteroids. (5.1, 8.4)
If irritation develops in the presence of dermatological infections, the use of an appropriate antifungal or antibacterial agent should be instituted. If a favorable response does not occur promptly, use of CLOBEX Shampoo should be discontinued until the infection has been adequately controlled. (5.3)
Local adverse reactions with topical corticosteroids may occur more frequently with the use of occlusive dressings and higher potency corticosteroids, including clobetasol propionate. These reactions include: folliculitis, acneiform eruptions, hypopigmentation, perioral dermatitis, allergic contact dermatitis, secondary infection, striae and miliaria. (5.4)

6 ADVERSE REACTIONS

The most common adverse reactions are burning/stinging, pruritus, edema, folliculitis, acne, dry skin, irritant dermatitis, alopecia, urticaria, skin atrophy and telangiectasia. (6.1)
To report SUSPECTED ADVERSE REACTIONS, contact Galderma Laboratories, L.P. at 1-866-735-4137 or FDA at 1-800-FDA-1088 or www.fda.gov/medwatch.

FULL PRESCRIBING INFORMATION

1 INDICATIONS AND USAGE

1.1 Indication

CLOBEX Shampoo, 0.05%, is a super-high potent topical corticosteroid formulation indicated for the treatment of moderate to severe forms of scalp psoriasis in subjects 18 years of age and older. Treatment should be limited to 4 consecutive weeks. The total dosage should not exceed 50 g (50 mL or 1.75 fl. oz.) per week.
Patients should be instructed to use CLOBEX Shampoo, 0.05%, for the minimum time period necessary to achieve the desired results [ see Dosage and Administration (2) ].
Use in patients younger than 18 years of age is not recommended due to numerically high rates of hypothalamic-pituitary-adrenal (HPA) axis suppression [ see Warnings and Precautions (5.1) and Use in Specific Populations (8.4) ].

1.2 Limitations of Use

CLOBEX Shampoo, 0.05%, should not be used on the face, groin or axillae. Avoid any contact of the drug product with the eyes and lips. In case of contact, rinse thoroughly with water all parts of the body that came in contact with the shampoo.

2 DOSAGE AND ADMINISTRATION

CLOBEX Shampoo, 0.05% is for topical use only, and not for ophthalmic, oral or intravaginal use.
CLOBEX Shampoo, 0.05%, should be applied onto dry (not wet) scalp once a day in a thin film to the affected areas only, and left in place for 15 minutes before lathering and rinsing.
The total dosage should not exceed 50 g (50 mL or 1.75 fl. oz.) per week.
Move the hair away from the scalp so that one of the affected areas is exposed. Position the bottle over the lesion. Apply a small amount of the shampoo directly onto the lesion, letting the product naturally flow from the bottle (gently squeeze the bottle), avoiding any contact of the product with the facial skin, eyes or lips. In case of contact, rinse thoroughly with water. Spread the product so that the entire lesion is covered with a thin uniform film. Massage gently into the lesion and repeat for additional lesion(s). Wash your hands after applying CLOBEX Shampoo, 0.05%.
Leave the shampoo in place for 15 minutes, then add water, lather and rinse thoroughly all parts of the scalp and body that came in contact with the shampoo (e.g., hands, face, neck and shoulders). Avoid contact with eyes and lips. Minimize contact to non-affected areas of the body. Although no additional shampoo is necessary to cleanse your hair, you may use a non-medicated shampoo if desired.
Treatment should be limited to 4 consecutive weeks. As with other corticosteroids, therapy should be discontinued when control is achieved. If complete disease control is not achieved after 4 weeks of treatment with CLOBEX Shampoo, 0.05%, treatment with a less potent topical steroid may be substituted. If no improvement is seen within 4 weeks, reassessment of the diagnosis may be necessary.
CLOBEX Shampoo, 0.05%, should not be used with occlusive dressings (shower cap or bathing cap) unless directed by a physician.

3 DOSAGE FORMS AND STRENGTHS

Shampoo, 0.05%, w/w. Each gram of CLOBEX Shampoo, 0.05%, contains 0.5 mg of clobetasol propionate in a translucent, colorless to pale yellow viscous liquid.

4 CONTRAINDICATIONS

None

5 WARNINGS AND PRECAUTIONS

5.1 Effects on the Endocrine System

Clobetasol propionate is a highly potent topical corticosteroid that has been shown to suppress the HPA axis at the lowest doses tested.
Systemic absorption of topical corticosteroids can produce reversible hypothalamic-pituitary-adrenal (HPA) axis suppression with the potential for clinical glucocorticosteroid insufficiency. This may occur during treatment or upon withdrawal of the topical corticosteroid.
The effect of CLOBEX (clobetasol propionate) Shampoo, 0.05% on HPA axis suppression was evaluated in one trial in adolescents 12 to 17 years of age. In this trial, 5 of 12 evaluable subjects developed suppression of their HPA axis following 4 weeks of treatment with CLOBEX (clobetasol propionate) Shampoo, 0.05% applied once daily for 15 minutes to a dry scalp before lathering and rinsing.
Because of the potential for systemic absorption, use of topical corticosteroids may require that patients be periodically evaluated for HPA axis suppression. Factors that predispose a patient using a topical corticosteroid to HPA axis suppression include the use of more potent steroids, use over large surface areas, use over prolonged periods, use under occlusion, use on an altered skin barrier, and use in patients with liver failure.
An adrenocorticotropic hormone (ACTH) stimulation test may be helpful in evaluating patients for HPA axis suppression. If HPA axis suppression is documented, an attempt should be made to gradually withdraw the drug, to reduce the frequency of application, or to substitute a less potent steroid. Manifestations of adrenal insufficiency may require supplemental systemic corticosteroids. Recovery of HPA axis function is generally prompt and complete upon discontinuation of topical corticosteroids.
Cushing’s syndrome, hyperglycemia, and unmasking of latent diabetes mellitus can also result from systemic absorption of topical corticosteroids.
Use of more than one corticosteroid-containing product at the same time may increase the total systemic exposure.
Pediatric patients may be more susceptible to systemic toxicity from equivalent doses due to their larger skin surface to body mass ratios [ see Use in Specific Populations (8.4) ].

5.2 Allergic Contact Dermatitis

If irritation develops, CLOBEX Shampoo, 0.05%, should be discontinued and appropriate therapy instituted. Allergic contact dermatitis with corticosteroids is usually diagnosed by observing a failure to heal rather than noting a clinical exacerbation. Clinical diagnosis of allergic contact dermatitis can be confirmed with patch testing.

5.3 Concomitant Skin Infections

In the presence of dermatologic infections, the use of an appropriate antifungal or antibacterial agent should be instituted. If a favorable response does not occur promptly, use of CLOBEX Shampoo, 0.05%, should be discontinued until the infection has been adequately controlled.

5.4 Local Adverse Reactions with Topical Corticosteroids

Local adverse reactions may be more likely to occur with occlusive use, prolonged use or use of higher potency corticosteroids.
Reactions may include atrophy, striae, telangiectasias, burning, itching, irritation, dryness, folliculitis, acneiform eruptions, hypopigmentation, perioral dermatitis, allergic contact dermatitis, secondary infection, and miliaria. Some local adverse reactions may be irreversible. Clobetasol propionate is not recommended in patients with acne vulgaris, rosacea or perioral dermatitis.

6 ADVERSE REACTIONS

6.1 Clinical Trials Experience

Because clinical trials are conducted under widely varying conditions, adverse reaction rates observed in the clinical trials of a drug cannot be directly compared to rates in the clinical trials of another drug and may not reflect the rates observed in practice.
In clinical trials with CLOBEX Shampoo, 0.05%, the following adverse reactions have been reported: headache, burning/stinging, pruritus, edema, folliculitis, acne, dry skin, irritant dermatitis, alopecia, urticaria, skin atrophy and telangiectasia.
Table 1 summarizes selected adverse reactions that occurred in at least1% of subjects in the Phase 2 and 3 studies for scalp psoriasis.

Table 1: Summary of Selected Averse Reactions ≥ 1% by Body System
Body System | Clobex Shampoo, 0.05% N=558 | Vehicle Shampoo N=127
Skin and Appendages | 49 (8.8%) | 28 (22.0%)
Discomfort Skin | 26 (4.7%) | 16 (12.6%)
Pruritus | 3 (0.5%) | 9 (7.1%)
Body as a Whole | 33 (5.9%) | 12 (9.4%)
Headache | 10 (1.8%) | 1 (0.8%)

Systemic absorption of topical corticosteroids has produced reversible HPA axis suppression, manifestations of Cushing's syndrome, hyperglycemia, and glucosuria in some patients.

6.2 Postmarketing Experience

Because these reactions are reported voluntarily from a population of uncertain size, it is not always possible to reliably estimate their frequency or establish a causal relationship to drug exposure. The following adverse reactions have been identified during post-approval use of CLOBEX Shampoo, 0.05%.

- Endocrine disorders:Cushing’s syndrome, Adrenal suppression
- Eye:Eye pain, Vision blurred, Eye irritation
- CNS:Dizziness
- GI:Nausea
- Skin:Erythema, Skin exfoliation, Rash, Skin irritation, Hair color changes, Allergic contact dermatitis, Pain of skin, Skin tightness
- Other:Psoriasis (aggravation)

8 USE IN SPECIFIC POPULATIONS

8.1 Pregnancy

Teratogenic effects: Pregnancy Category C.
There are no adequate and well-controlled studies in pregnant women. Therefore, CLOBEX Shampoo, 0.05% should be used during pregnancy only if the potential benefit justifies the potential risk to the fetus.
Corticosteroids have been shown to be teratogenic in laboratory animals when administered systemically at relatively low dosage levels. Some corticosteroids have been shown to be teratogenic after dermal application to laboratory animals.
Clobetasol propionate is absorbed percutaneously, and when administered subcutaneously it was a significant teratogen in both the rabbit and the mouse.
Clobetasol propionate has greater teratogenic potential than steroids that are less potent.
The effect of clobetasol propionate on pregnancy outcome and development of offspring was studied in the rat. Clobetasol propionate was administered subcutaneously to female rats twice daily (0, 12.5, 25, and 50 µg/kg/day) from day 7 of presumed gestation through day 25 of lactation or day 24 presumed gestation for those rats that did not deliver a litter. The maternal no-observed-effect-level (NOEL) for clobetasol propionate was less than 12.5 μg/kg/day due to reduced body weight gain and feed consumption during the gestation period. The reproductive NOEL in the dams was 25 μg/kg/day (ratio of animal dose to proposed human dose of 0.07 on a mg/m ^2/day basis) based on prolonged delivery at a higher dose level. The no-observed-adverse-effect-level (NOAEL) for viability and growth in the offspring was 12.5 μg/kg/day (ratio of animal dose to proposed human dose of 0.03 on a mg/m ^2/day basis) based on incidence of stillbirths, reductions in pup body weights on days 1 and 7 of lactation, increased pup mortality, increases in the incidence of umbilical hernia, and increases in the incidence of pups with cysts on the kidney at higher dose levels during the preweaning period. The weights of the epididymides and testes were significantly reduced at higher dosages. Despite these changes, there were no effects on the mating and fertility of the offspring.

8.3 Nursing Mothers

Systemically administered corticosteroids appear in human milk and could suppress growth, interfere with endogenous corticosteroid production, or cause other untoward effects. It is not known whether topical administration of corticosteroids could result in sufficient systemic absorption to produce detectable quantities in human milk. Because many drugs are excreted in human milk, caution should be exercised when CLOBEX Shampoo, 0.05%, is administered to a nursing woman.

8.4 Pediatric Use

Use of CLOBEX Shampoo, 0.05%, in patients under 18 years old is not recommended due to potential for HPA axis suppression [ see Warnings and Precautions (5.1) ].
The effect of CLOBEX (clobetasol propionate) Shampoo, 0.05%, on HPA axis suppression was evaluated in one trial in adolescents 12 to 17 years of age with moderate to severe scalp psoriasis with involvement of at least 25% of the scalp. In this trial, 5 of 12 evaluable subjects developed suppression of their HPA axis following 4 weeks of treatment with CLOBEX (clobetasol propionate) Shampoo, 0.05%, applied once daily for 15 minutes to a dry scalp before lathering and rinsing. Only 1 of the 5 subjects who had suppression was tested for recovery of HPA axis, and this subject recovered after 2 weeks.
No studies have been performed in patients under the age of 12. Because of a higher ratio of skin surface area to body mass, pediatric patients are at a greater risk than adults of HPA axis suppression and Cushing’s syndrome when they are treated with topical corticosteroids. They are therefore also at greater risk of adrenal insufficiency during and/or after withdrawal of treatment. Adverse effects including striae have been reported with inappropriate use of topical corticosteroids in infants and children. Therefore, use is not recommended in patients under the age of 18.
HPA axis suppression, Cushing’s syndrome, linear growth retardation, delayed weight gain, and intracranial hypertension have been reported in children receiving topical corticosteroids. Manifestations of adrenal suppression in children include low plasma cortisol levels and an absence of response to ACTH stimulation. Manifestations of intracranial hypertension include bulging fontanelles, headaches, and bilateral papilledema.

8.5 Geriatric Use

Clinical studies of CLOBEX Shampoo, 0.05%, did not include sufficient numbers of subjects aged 65 and over to determine whether they respond differently than younger subjects. In general, dose selection for an elderly patient should be made with caution, usually starting at the low end of the dosing range, reflecting the greater frequency of decreased hepatic, renal or cardiac function, and of concomitant disease or other drug therapy.

10 OVERDOSAGE

Topically applied, CLOBEX Shampoo, 0.05%, can be absorbed in sufficient amounts to produce systemic effects [ see Warnings and Precautions (5.1) ].

11 DESCRIPTION

CLOBEX (clobetasol propionate) Shampoo, 0.05%, contains clobetasol propionate, a synthetic fluorinated corticosteroid, for topical use. The corticosteroids constitute a class of primarily synthetic steroids used topically as anti-inflammatory and antipruritic agents.
The chemical name of clobetasol propionate is 21-chloro-9-fluoro-11β, 17-dihydroxy-16β-methylpregna-1, 4-diene-3, 20-dione 17-propionate.

It has the following structural formula:

Clobetasol propionate has a molecular weight of 466.97 (CAS Registry Number 25122-46-7). The molecular formula is C 25H 32CIFO 5. Clobetasol propionate is a white to practically white crystalline, odorless powder insoluble in water.
Each gram of CLOBEX (clobetasol propionate) Shampoo, 0.05%, contains 0.5 mg of clobetasol propionate in a translucent, colorless to pale yellow viscous liquid shampoo base consisting of alcohol, citric acid, coco-betaine, polyquaternium-10, purified water, sodium citrate, and sodium laureth sulfate.

12 CLINICAL PHARMACOLOGY

12.1 Mechanism of Action

Like other topical corticosteroids, CLOBEX (clobetasol propionate) Shampoo, 0.05%, has anti-inflammatory, antipruritic, and vasoconstrictive properties. The mechanism of the anti-inflammatory activity of the topical steroids, in general, is unclear. However, corticosteroids are thought to act by the induction of phospholipase A 2inhibitory proteins, collectively called lipocortins. It is postulated that these proteins control the biosynthesis of potent mediators of inflammation such as prostaglandins and leukotrienes by inhibiting the release of their common precursor, arachidonic acid. Arachidonic acid is released from membrane phospholipids by phospholipase A 2.

12.2 Pharmacodynamics

Vasoconstrictor Assay
CLOBEX Shampoo, 0.05%, is in the super-high range of potency as demonstrated in vasoconstrictor studies in healthy subjects when compared with other topical corticosteroids. However, similar blanching scores do not necessarily imply therapeutic equivalence.
Hypothalamic-Pituitary-Adrenal (HPA) Axis Suppression
In studies evaluating the potential for hypothalamic-pituitary-adrenal (HPA) axis suppression, use of CLOBEX (clobetasol propionate) Shampoo, 0.05%, resulted in demonstrable HPA axis suppression in 5 out of 12 (42%) adolescent subjects [ see Warnings and Precautions (5.1) and Use in Specific Populations (8.4) ].

12.3 Pharmacokinetics

The extent of percutaneous absorption of topical corticosteroids is determined by many factors, including the vehicle, the integrity of the epidermal barrier and occlusion.
Topical corticosteroids can be absorbed from normal intact skin. Inflammation and other disease processes in the skin may increase percutaneous absorption.
There are no human data regarding the distribution of corticosteroids to body organs following topical application. Nevertheless, once absorbed through the skin, topical corticosteroids are handled through metabolic pathways similar to systemically administered corticosteroids. They are metabolized, primarily in the liver, and are then excreted by the kidneys. In addition, some corticosteroids and their metabolites are also excreted in the bile.

13 NONCLINICAL TOXICOLOGY

13.1 Carcinogenesis, Mutagenesis, Impairment of Fertility

Clobetasol propionate was not carcinogenic to rats when topically applied for 2 years at concentrations up to 0.005% which corresponded to doses up to 11 µg/kg/day (ratio of animal dose to proposed human dose of 0.03 on a mg/m ^2/day basis).
Clobetasol propionate at concentrations up to 0.001% did not increase the rate of formation of ultra violet light-induced skin tumors when topically applied to hairless mice 5 days per week for a period of 40 weeks.
Clobetasol propionate was negative in the in vitromammalian chromosomal aberration test and in the in vivomammalian erythrocyte micronucleus test.
The effect of subcutaneously administered clobetasol propionate on fertility and general reproductive toxicity was studied in rats at doses of 0, 12.5, 25, and 50 µg/kg/day. Males were treated beginning 70 days before mating and females beginning 15 days before mating through day 7 of gestation. A dosage level of less than 12.5 µg/kg/day clobetasol propionate was considered to be the no-observed-effect-level (NOEL) for paternal and maternal general toxicity based on decreased weight gain and for male reproductive toxicity based on increased weights of the seminal vesicles. The female reproductive NOEL was 12.5 µg/kg/day (ratio of animal dose to proposed human dose of 0.03 on a mg/m ^2/day basis) based on reduction in the numbers of estrous cycles during the pre-cohabitation period and an increase in the number of nonviable embryos at higher doses.

14 CLINICAL STUDIES

The safety and efficacy of CLOBEX Shampoo, 0.05%, have been evaluated in two clinical trials involving 290 subjects with moderate to severe scalp psoriasis. In both trials, subjects were treated with either CLOBEX Shampoo or the corresponding vehicle applied once daily for 15 minutes before lathering and rinsing for a period of 4 weeks. Efficacy results are presented in Table 2 below.

Table 2: Efficacy Results | CLOBEX Shampoo, 0.05% N (%) |  | Shampoo Vehicle n (%)
 | Study A | Study B | Study A | Study B
Total Number of Subjects | 95 | 99 | 47 | 49
Success Rate ^1at Endpoint ^2 | 40 (42.1%) | 28 (28.3%) | 1 (2.1%) | 5 (10.2%)
Subjects with Scalp Psoriasis Parameter Clear (None) at Endpoint Erythema ^3 Scaling ^3 Plaque Thickening ^3 | 17 (17.9%) 21 (22.1%) 35 (36.8%) | 12 (12.1%) 15 (15.2%) 34 (34.3%) | 3 (6.4%) 0 (0%) 5 (10.6%) | 1 (2.0%) 2 (4.1%) 5 (10.2%)

^1Success rate defined as the proportion of subjects with a-0 (clear) or 1 (minimal) on a 0 to 5 point physician's Global Severity Scale for scalp psoriasis.
^2At four (4) weeks or last observation recorded for a subject during the treatment period (baseline if no post-baseline data were available).
^3Subjects with 0 (clear) on a 0 to 3 point scalp psoriasis parameter scale.
Clinical studies of CLOBEX Shampoo, 0.05%, did not include sufficient numbers of non-Caucasian subjects to determine whether they respond differently than Caucasian subjects with regards to efficacy and safety.

16 HOW SUPPLIED/STORAGE AND HANDLING

CLOBEX Shampoo, 0.05%, is a translucent, colorless to pale yellow viscous liquid, supplied in 4 fl. oz. (118 mL) bottles.

NDC0299-3847-04
Storage:Keep tightly closed. Store at USP controlled room temperature 68˚ to 77˚F (20˚ - 25˚C), with excursions permitted between 59˚ and 86˚F (15˚ - 30˚C).

17 PATIENT COUNSELING INFORMATION

See FDA-approved patient labeling (Patient Information)

Information for Patients
Inform the patient using topical corticosteroids to adhere to following instructions:

- This medication is to be used as directed by the physician and should not be used longer than the prescribed time period.
- CLOBEX Shampoo, 0.05%, is for external use only. It should not be used on the face, underarms or groin areas. Avoid contact with the eyes and lips.
- This medication should not be used for any disorder other than that for which it was prescribed.
- The scalp area should not be covered while the medication is on the scalp (e.g., shower cap, bathing cap) so as to be occlusive unless directed by the physician.
- Patients should report any signs of local or systemic adverse reactions to their physician.
- As with other corticosteroids, therapy should be discontinued when control is achieved. If no improvement is seen within 4 weeks, contact the physician.
- Patients should wash their hands after applying the medication.
- Patients should inform their physician(s) that they are using CLOBEX Shampoo, 0.05%, if surgery is contemplated.
- Do not use other corticosteroid-containing products while using CLOBEX Shampoo, 0.05%.
- Patients should not use more than 50 g (50 mL or 1.75 fl. oz.) per week of CLOBEX Shampoo, 0.05%.

Patient Information
CLOBEX® (Klo-bex)
(clobetasol propionate)
Shampoo
Important:For use on the scalp only. Do not get CLOBEX Shampoo near or in your eyes, mouth or vagina.
Read the Patient Information that comes with CLOBEX Shampoo before you start using it and each time you get a refill. There may be new information. This information does not take the place of talking with your doctor about your medical condition or your treatment.
What is CLOBEX Shampoo?

- CLOBEX Shampoo is a prescription corticosteroid medicine used to treat adults with moderate to severe forms of scalp psoriasis. CLOBEX Shampoo is for use on the scalp only (topical).
- CLOBEX Shampoo should be used for the shortest amount of time needed to treat your scalp psoriasis.
- You should not use CLOBEX Shampoo for longer than 4 weeks in a row.
- You should not use more than 50 mL (1.75 fluid ounces) of CLOBEX Shampoo in one week.

You should not use CLOBEX Shampoo:

- on your face, underarms (armpits) or groin areas. Avoid getting CLOBEX Shampoo in your eyes or on your lips.

CLOBEX Shampoo should not be used in children under 18 years of age.
What should I tell my doctor before using CLOBEX Shampoo?
Before you use CLOBEX Shampoo, tell your doctor if you:

- have a scalp infection. You may need medicine to treat the scalp infection before you use CLOBEX Shampoo.
- have any open sores or cuts on your scalp
- plan to have surgery
- have acne vulgaris, rosacea, or a rash around your mouth (perioral dermatitis)
- have any other medical conditions
- are pregnant or plan to become pregnant. It is not known if CLOBEX Shampoo can harm your unborn baby.
- are breast-feeding or plan to breast-feed. It is not known if CLOBEX Shampoo passes into your breast milk.

Talk to your doctor about the best way to feed your baby if you use CLOBEX Shampoo.

Tell your doctor about all the medicines you take,including prescription and non-prescription medicines, vitamins, and herbal supplements. Especially tell your doctor if you take other corticosteroid medicines by mouth or use other products on your skin that contain corticosteroids. You should not use other products that contain corticosteroids while you are using CLOBEX Shampoo. Ask your doctor or pharmacist if you are not sure.
Know the medicines you take. Keep a list of them to show your doctor and pharmacist if you get a new medicine.
How should I use CLOBEX Shampoo?

- Use CLOBEX Shampoo exactly as your doctor tells you to use it.
- Your doctor should tell you how much CLOBEX Shampoo to use and where to apply it.
- CLOBEX Shampoo is for use on your scalp only (topical).
- Apply CLOBEX Shampoo on affected areas of your scalp one time each day.
- Use only enough CLOBEX Shampoo to cover the affected areas of your scalp.
- Do not use CLOBEX Shampoo on your face, groin, or underarms. Avoid getting CLOBEX Shampoo in your eyes or on your lips.
- Do not wet your hair before using CLOBEX Shampoo.
- If CLOBEX Shampoo gets on any part of your body other than your scalp, rinse the area well with water.
- You should not bandage or cover your head with a shower cap, bathing cap, or a towel, while CLOBEX Shampoo is on your scalp, unless your doctor tells you to.
- Tell your doctor if your scalp condition is not getting better after 4 weeks of using CLOBEX Shampoo. You should not use CLOBEX Shampoo for more than 4 weeks unless your doctor tells you to.

See the “Instructions for Use” at the end of the Patient Information for detailed information about the right way to use CLOBEX Shampoo.
What are the possible side effects of CLOBEX Shampoo?
CLOBEX Shampoo can pass through your skin.Too much CLOBEX Shampoo passing through your skin can cause your adrenal glands to stop working. Your doctor may do blood tests to check how well your adrenal glands are working.
The most common side effects of CLOBEX Shampoo include:

- burning or stinging at the site of application
- itching
- swelling
- inflamed hair follicle
- acne
- dry, itchy and reddened skin
- hair loss
- rash or hives
- thinning of the skin
- widening of small blood vessels in the skin

If you go to another doctor for illness, injury or surgery, tell that doctor that you are using CLOBEX Shampoo.
Tell your doctor if you have any side effect that bothers you or that does not go away.
These are not all the possible side effects of CLOBEX Shampoo. For more information, ask your doctor or pharmacist.
Call your doctor for medical advice about side effects. You may report side effects to FDA at 1-800-FDA-1088.
You may also report side effects to Galderma Laboratories, L.P. at 1-866-735-4137.
How should I store CLOBEX Shampoo?

- Store CLOBEX Shampoo at room temperature between 68˚F to 77˚F (20˚C to 25˚C).
- Keep the CLOBEX Shampoo bottle tightly closed.

Keep CLOBEX Shampoo and all medicines out of the reach of children.
General information about CLOBEX Shampoo
Medicines are sometimes prescribed for purposes other than those listed in a Patient Information leaflet. Do not use CLOBEX Shampoo for a condition for which it was not prescribed. Do not give CLOBEX Shampoo to other people, even if they have the same symptoms that you have. It may harm them.
This Patient Information leaflet summarizes the most important information about CLOBEX Shampoo. If you would like more information, talk with your doctor. You can ask your pharmacist or doctor for information about CLOBEX Shampoo that is written for health professionals.
What are the ingredients in CLOBEX Shampoo?
Active ingredient: clobetasol propionate
Inactive ingredients (shampoo base): alcohol, citric acid, coco-betaine, polyquaternium-10, purified water, sodium citrate and sodium laureth sulfate.
Instructions for Use
CLOBEX® (KLO-bex)
(clobetasol propionate)
Shampoo

Important:For use on the scalp only. Do not get CLOBEX Shampoo near or in your eyes, mouth or vagina.

Read the Instructions for Use that comes with CLOBEX Shampoo before you start using it and each time you get a refill. There may be new information. This information does not take the place of talking with your doctor about your medical condition or your treatment.
How to apply CLOBEX Shampoo to your scalp:
Your hair should be dry when you apply CLOBEX Shampoo to your scalp.
Do not get CLOBEX Shampoo on your face, in your eyes or on your lips.If CLOBEX Shampoo does get on these areas, rinse well with water.
Step 1: To apply CLOBEX Shampoo to your scalp, part your hair at the area where it is to be applied.
Step 2: Hold the bottle of CLOBEX Shampoo over the affected area. Gently squeeze the bottle and apply a small amount of shampoo to the affected area.
Step 3: Gently rub CLOBEX Shampoo into the affected area so that only the affected area is covered with a thin, even layer of CLOBEX Shampoo.
Step 4: Repeat Steps 1 through 3 to apply CLOBEX Shampoo to other affected areas on your scalp as instructed by your doctor.
Step 5: Wash your hands after applying CLOBEX Shampoo.
Step 6 : Leave CLOBEX Shampoo on your scalp for 15 minutes. You should not bandage or cover your head with a shower cap, bathing cap, or a towelwhile CLOBEX Shampoo is on your scalp, unless your doctor tells you to.
Step 7: After 15 minutes have passed, wet your hair with water. Lather and rinse your hair and scalp completely. Rinse any other parts of your body that come into contact with CLOBEX Shampoo, such as your hands, face, neck and shoulders.
No other shampoo is needed, but you may wash your hair with a non-medicated shampoo after using CLOBEX Shampoo.
This Patient Information and Instructions for Use have been approved by the U.S. Food and Drug Administration.
Marketed by:
GALDERMA LABORATORIES, L.P.
Dallas, TX 75201 USA
P51352-3
Manufactured by:
G Production Inc., Baie d’Urfé, QC, H9X 3S4 Canada

All trademarks are the property of their resective owners.
US Patent Nos. 7,316,810 and 7,700,081

PACKAGE LABEL

Rx Only

NDC 0299-3847-04

Clobex ®
(clobetasol propionate)
SHAMPOO
0.05%

4 FL OZ
(118 mL)

GALDERMA

For External Use Only.

Not for Ophthalmic Use.

Usual dosage: Apply a thin film to affected areas of the scalp once daily; apply on dry scalp and leave in place for 15 minutes before lathering and rinsing.
Do not apply CLOBEX ® (clobetasol propionate) Shampoo, 0.05% to the face, underarms or groin, and avoid contact with eyes and lips. Do not use for longer than 4 weeks. See package insert for complete prescribing information.
See carton closure for lot number and expiration date .

Each mL contains:
Active ingredient:clobetasol propionate, 0.05%.

Excipients:alcohol, citric acid, coco-betaine, polyquaternium-10, purified water, sodium citrate, and sodium laureth sulfate.

Storage:Keep tightly closed. Store at controlled room temperature 68° to 77°F (20°- 25°C) with excursions permitted between 59° to 86°F (15°- 30°C).

GALDERMA
Marketed by:
Galderma Laboratories, L.P.
Dallas, Texas 75201 USA
Made in Canada
All trademarks are the property of their respective owners.
P51351-4